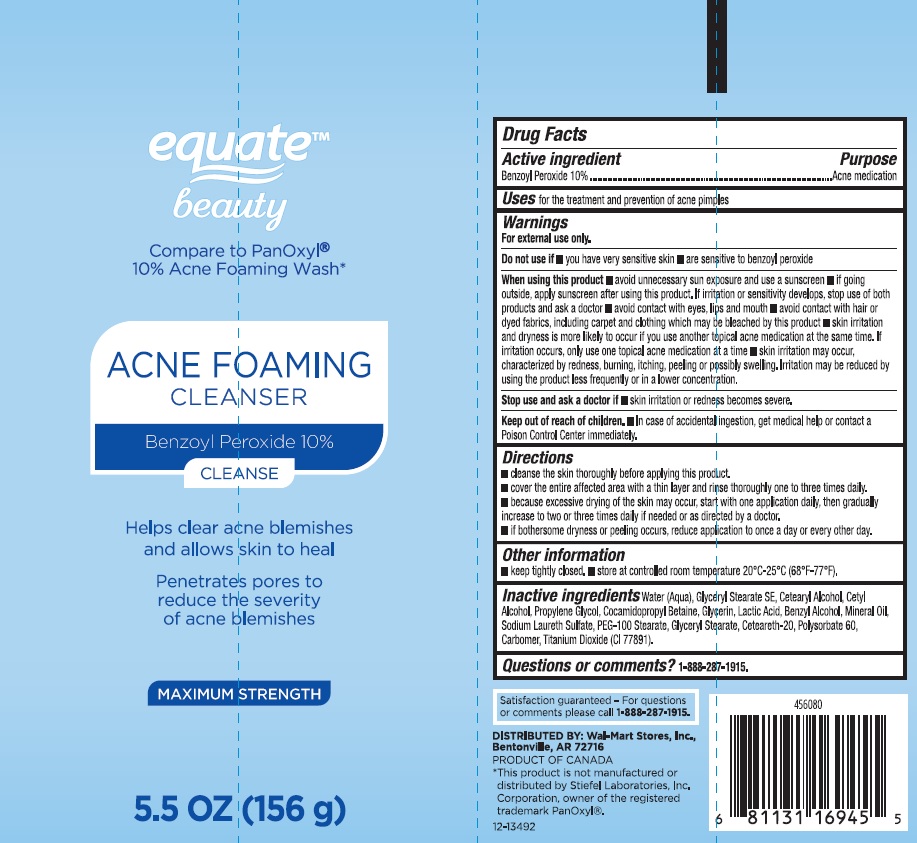 DRUG LABEL: Equate Beauty Acne Foaming Cleanser
NDC: 49035-132 | Form: LIQUID
Manufacturer: Wal-Mart Stores Inc
Category: otc | Type: HUMAN OTC DRUG LABEL
Date: 20170714

ACTIVE INGREDIENTS: BENZOYL PEROXIDE 0.1 mg/1 g
INACTIVE INGREDIENTS: WATER; GLYCERYL STEARATE SE; CETOSTEARYL ALCOHOL; CETYL ALCOHOL; PROPYLENE GLYCOL; COCAMIDOPROPYL BETAINE; GLYCERIN; LACTIC ACID; BENZYL ALCOHOL; MINERAL OIL; SODIUM LAURETH SULFATE; PEG-100 STEARATE; GLYCERYL MONOSTEARATE; POLYOXYL 20 CETOSTEARYL ETHER; POLYSORBATE 60; CARBOMER 934; TITANIUM DIOXIDE

DRUG FACTS

Active ingredient

Benzoyl Peroxide 10%

Purpose

Acne medication

Uses

for the treatment and prevention of acne pimples

Warnings

For external use only.

Do not use if

- you have very sensitive skin
- are sensitive to benzoyl peroxide

When using this product

- avoid unnecessary sun exposure and use a sunscreen
- if going outside, apply sunscreen after using this product. If irritation or sensitivity develops, stop use of both products and ask a doctor
- avoid contact with eyes, lips and mouth
- avoid contact with hair or dyed fabrics, including carpet and clothing which may be bleached by this product
- skin irritation and dryness is more likely to occur if you use another topical acne medication at the same time. If irritation occurs, only use one topical acne medication at a time
- skin irritation may occur, characterized by redness, burning, itching, peeling or possibly swelling. Irritation may be reduced by using the product less frequently or in a lower concentration

Stop use and ask a doctor if

- skin irritation or redness becomes severe.

Keep out of reach of children.

- In case of accidental ingestion, get medical help or contact a Poison Control Center immediately.

Directions

- cleanse the skin thoroughly before applying this product
- cover the entire affected area with a thin layer and rinse thoroughly one to three times daily
- because excessive drying of the skin may occur, start with one application daily, then gradually increase to two or three times daily if needed or as directed by a doctor.
- if bothersome dryness or peeling occurs, reduce application to once a day or every other day

Other information

- keep tightly closed
- store at controlled room temperature 20°C-25°C (68°F-77°F)

Inactive ingredients

Water (Aqua), Glyceryl Stearate SE, Cetearyl Alcohol, Cetyl Alcohol, Propylene Glycol, Cocamidopropyl Betaine, Glycerin, Lactic Acid, Benzyl Alcohol, Mineral Oil, Sodium Laureth Sulfate, PEG-100 Stearate, Glyceryl Stearate, Ceteareth-20, Polysorbate 60, Carbomer, Titanium Dioxide (CI 77891).

Questions or comments?

1-888-287-1915